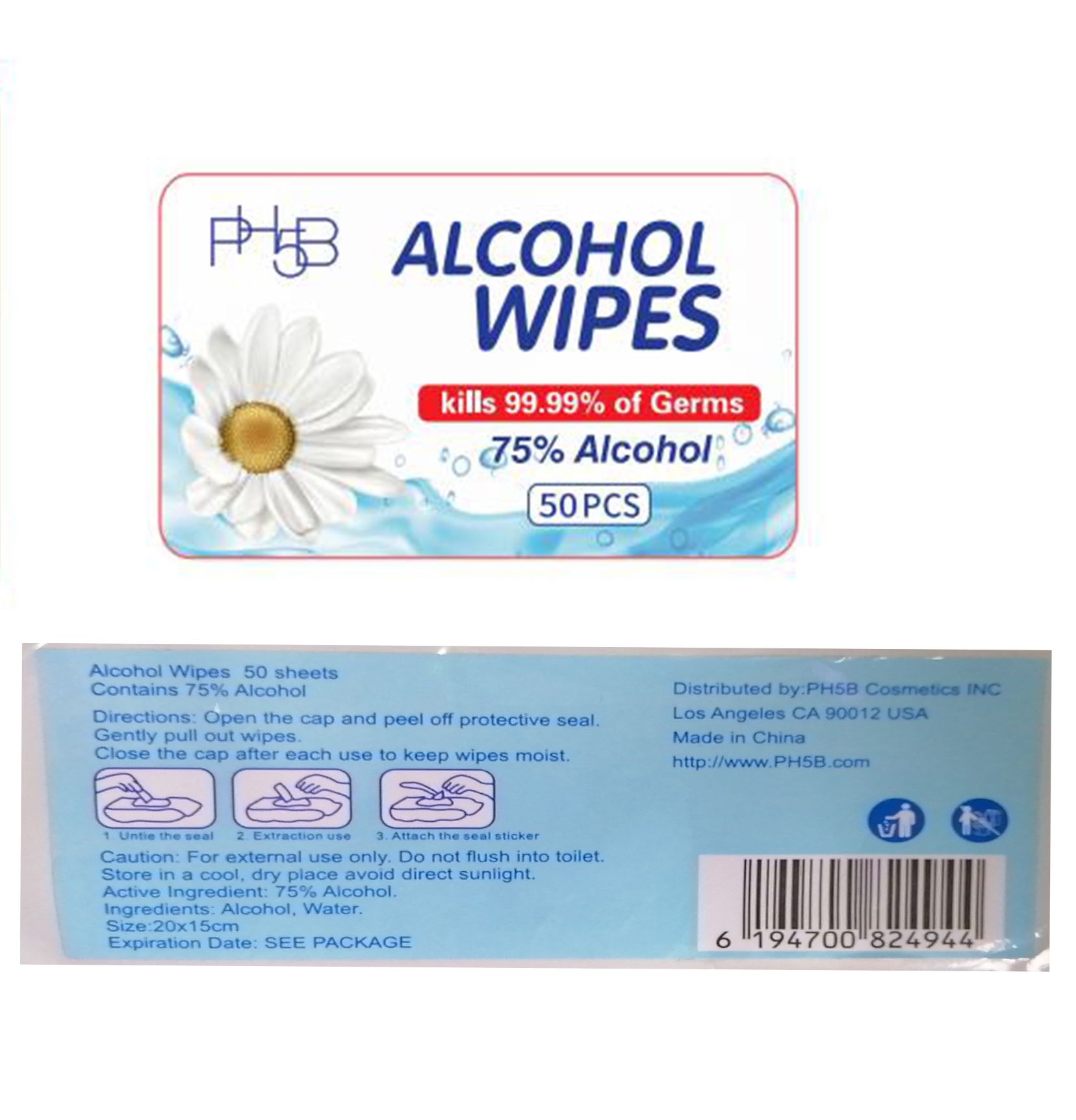 DRUG LABEL: PH5B Alcohol Wipes
NDC: 76718-008 | Form: SWAB
Manufacturer: Guangzhou Jukang Sanitary Products Co., Ltd.
Category: otc | Type: HUMAN OTC DRUG LABEL
Date: 20200425

ACTIVE INGREDIENTS: ALCOHOL 75 g/100 g
INACTIVE INGREDIENTS: WATER

Antibacterial Wipes

Active Ingredient

Ethanol 75% by volume

Purpose

Antiseptic

USE

●For hand sanitizing to decrease bacteria on the skin.
●Apply topically to the skin to help prevent cross contamination.
●Recommended for repeated use.
●Dries in seconds.

Warning

- Flammable, keep away from fire or flame. For external use only.
- Do not flush into toilet.
- store in a cool, dry place avoid direct sunlight.

●Keep out of reach of children unless under adult supervision. If swallowed, get medical help or contact a Poison Contrl Center immediately.

Directions

●Open the cap and peel off protctive seal. Gently pull out wips.
●Clos the cap after each use to keep wipes moist.

Inactive ingredients

Aqua.